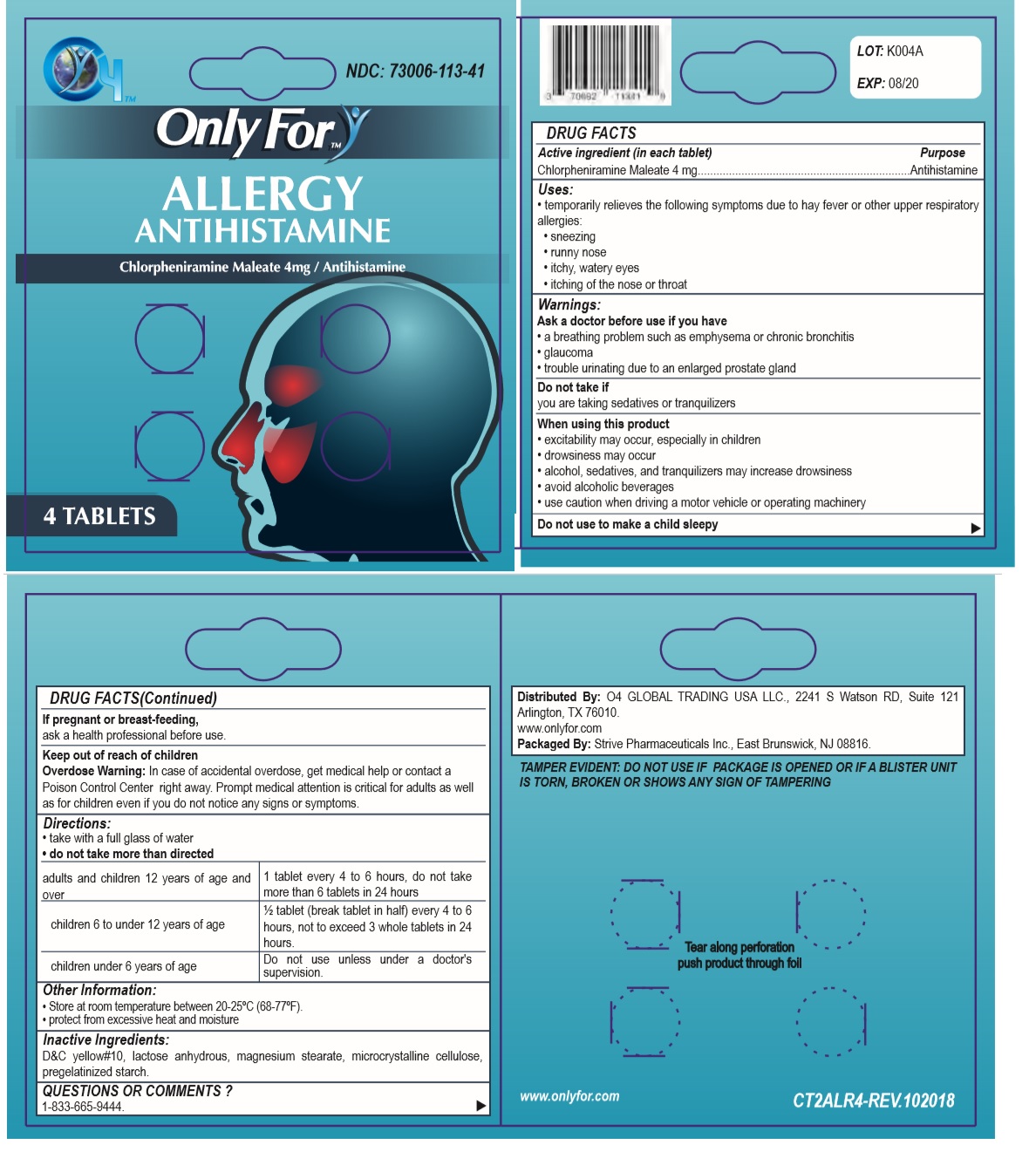 DRUG LABEL: Only For
NDC: 73006-113 | Form: TABLET
Manufacturer: O4 Global Trading Usa, Llc 
Category: otc | Type: HUMAN OTC DRUG LABEL
Date: 20190528

ACTIVE INGREDIENTS: CHLORPHENIRAMINE MALEATE 4 mg/1 1
INACTIVE INGREDIENTS: D&C YELLOW NO. 10; ANHYDROUS LACTOSE; MAGNESIUM PALMITOSTEARATE; MICROCRYSTALLINE CELLULOSE 101; STARCH, CORN

Only For- ALLERGY

Active ingredient (in each tablet)

Chlorpheniramine Maleate 4mg

Purpose

Antihistamine

Uses:

- temporarily relieves the following symptoms due to hay fever or other upper respiratory allergies:
- sneezing
- runny nose
- itchy, watery eyes
- itching of the nose or throat

Warnings:

Ask a doctor before use if you have

- a breathing problem such as emphysema or chronic bronchitis
- glaucoma
- trouble urinating due to an enlarged prostate gland

Do not take if
you are taking sedatives or tranquilizers

When using this product

- excitability may occur, especially in children
- drowsiness may occur
- alcohol, sedatives, and tranquilizers may increase drowsiness
- avoid alcoholic beverages
- use caution when driving a motor vehicle or operating machinery

Do not use to make a child sleepy

If pregnant or breast-feeding,
ask a health professional before use.

Keep out of reach of children

Overdose Warning: In case of accidental overdose, get medical help or contact a Poison Control Center right away. Prompt medical attention is critical for adults as well as for children even if you do not notice any signs or symptoms.

Directions:

- take with a full glass of water
- Do not take more than directed

adults and children 12 years of age and over | 1 tablet every 4 to 6 hours, do not take more than 6 tablets in 24 hours
children 6 to under 12 years of age | ½ tablet (break tablet in half) every 4 to 6 hours, not to exceed 3 whole tablets in 24 hours.
children under 6 years of age | ask a doctor

Other Information:

- Store at room temperature between 20-25°C (68-77°F).
- protect from excessive heat and moisture

Inactive Ingredients:

D&C yellow#10, lactose anhydrous, magnesium stearate, microcrystalline cellulose, pregelatinized starch.

QUESTIONS OR COMMENTS ?

1-833-665-9444.

NDC: 73006-113-41

ANTIHISTAMINE

Distributed By: O4 GLOBAL TRADING USA LLC., 2241 S Watson RD, Suite 121 Arlington, TX 76010.

www.onlyfor.com

Packaged By: Strive Pharmaceuticals Inc., East Brunswick, NJ 08816.

TAMPER EVIDENT: DO NOT USE IF PACKAGE IS OPENED OR IF A BLISTER UNIT IS TORN, BROKEN OR SHOWS ANY SIGN OF TAMPERING

Tear along perforation push product through foil